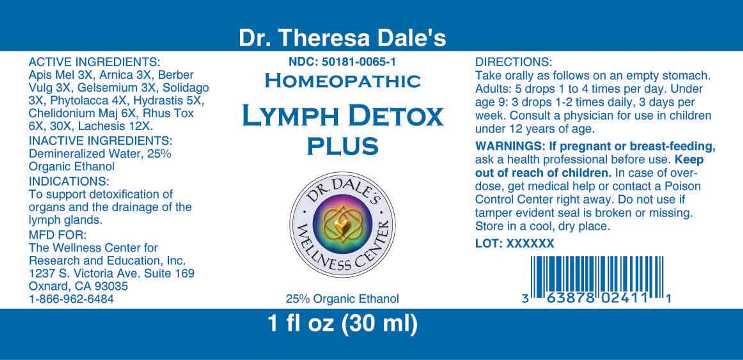 DRUG LABEL: Lymph Detox Plus
NDC: 50181-0065 | Form: LIQUID
Manufacturer: The Wellness Center for Research and Education, Inc.
Category: homeopathic | Type: HUMAN OTC DRUG LABEL
Date: 20250529

ACTIVE INGREDIENTS: APIS MELLIFERA 3 [hp_X]/1 mL; ARNICA MONTANA 3 [hp_X]/1 mL; BERBERIS VULGARIS ROOT BARK 3 [hp_X]/1 mL; GELSEMIUM SEMPERVIRENS ROOT 3 [hp_X]/1 mL; SOLIDAGO VIRGAUREA FLOWERING TOP 3 [hp_X]/1 mL; PHYTOLACCA AMERICANA ROOT 4 [hp_X]/1 mL; GOLDENSEAL 5 [hp_X]/1 mL; CHELIDONIUM MAJUS 6 [hp_X]/1 mL; TOXICODENDRON PUBESCENS LEAF 6 [hp_X]/1 mL; LACHESIS MUTA VENOM 12 [hp_X]/1 mL
INACTIVE INGREDIENTS: WATER; ALCOHOL

Drug Facts:

ACTIVE INGREDIENTS:

Apis Mellifica 3X, Arnica Montana 3X, Berberis Vulgaris 3X, Gelsemium Sempervirens 3X, Solidago Virgaurea 3X, Phytolacca Decandra 4X, Hydrastis Canadensis 5X, Chelidonium Majus 6X, Rhus Toxicodendron 6X, 30X, Lachesis Mutus 12X.

INDICATIONS:

To support detoxification of organs and the drainage of the lymph glands.

WARNINGS:

If pregnant or breast-feeding, ask a health professional before use.

Keep out of reach of children. In case of overdose, get medical help or contact a Poison Control Center right away.

Do not use if tamper evident seal is broken or missing.

Store in a cool, dry place.

Keep out of reach of children. In case of overdose, get medical help or contact a Poison Control Center right away.

DIRECTIONS:

Take orally as follows on an empty stomach.

Adults: 5 drops 1 to 4 times per day.

Under age 9: 3 drops 1-2 times daily, 3 days per week.

Consult a physician for use in children under 12 years of age.

INDICATIONS:

To support detoxification of organs and the drainage of the lymph glands.

INACTIVE INGREDIENTS:

Demineralized Water, 25% Organic Ethanol

QUESTIONS:

MFD FOR:

The Wellness Center for

Research and Education, Inc.

1237 S. Victoria Ave., Suite 169

Oxnard, CA 93035

1-866-962-6484

PACKAGE LABEL DISPLAY:

Dr. Theresa Dale's

NDC 50181-0065-1

HOMEOPATHIC

LYMPH DETOX

PLUS

1 fl oz (30 ml)